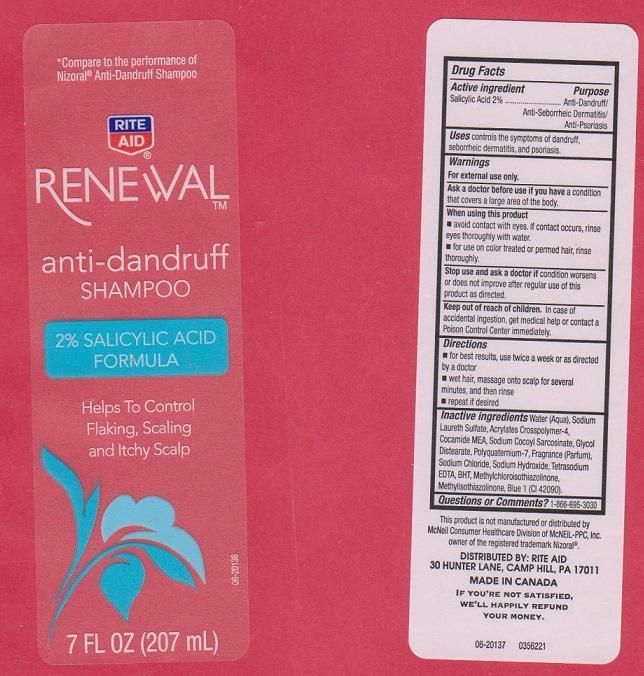 DRUG LABEL: RENEWAL
NDC: 11822-4500 | Form: LIQUID
Manufacturer: RITE AID CORPORATION
Category: otc | Type: HUMAN OTC DRUG LABEL
Date: 20141209

ACTIVE INGREDIENTS: SALICYLIC ACID 20 mg/1 mL
INACTIVE INGREDIENTS: WATER; SODIUM LAURETH SULFATE; CARBOMER COPOLYMER TYPE A (ALLYL PENTAERYTHRITOL CROSSLINKED); COCO MONOETHANOLAMIDE; SODIUM COCOYL SARCOSINATE; GLYCOL DISTEARATE; POLYQUATERNIUM-7 (70/30 ACRYLAMIDE/DADMAC; 1600000 MW); SODIUM CHLORIDE; SODIUM HYDROXIDE; EDETATE SODIUM; BUTYLATED HYDROXYTOLUENE; METHYLCHLOROISOTHIAZOLINONE; METHYLISOTHIAZOLINONE; FD&C BLUE NO. 1

DRUG FACTS

ACTIVE INGREDIENT

SALICYLIC ACID 2%

PURPOSE

ANTI-DANDRUFF/ ANTI-SEBORRHEIC DERMATITIS/ ANTI-PSORIASIS

USES

CONTROLS THE SYMPTOMS OF DANDRUFF, SEBORRHEIC DERMATITIS, AND PSORIASIS

WARNINGS

FOR EXTERNAL USE ONLY

ASK A DOCTOR BEFORE USE IF YOU HAVE

A CONDITION THAT COVERS A LARGE AREA OF THE BODY

WHEN USING THIS PRODUCT

- AVOID CONTACT WITH EYES. IF CONTACT OCCURS, RINSE EYES THOROUGHLY WITH WATER
- FOR USE ON COLOR TREATED OR PERMED HAIR, RINSE THOROUGHLY

STOP USE AND ASK A DOCTOR IF

CONDITION WORSENS OR DOES NOT IMPROVE AFTER REGULAR USE OF THIS PRODUCT AS DIRECTED

KEEP OUT OF REACH OF CHILDREN

IN CASE OF ACCIDENTAL INGESTION, GET MEDICAL HELP OR CONTACT A POISON CONTROL CENTER IMMEDIATELY

DIRECTIONS

- FOR BEST RESULTS, USE TWICE A WEEK OR AS DIRECTED BY A DOCTOR
- WET HAIR, MASSAGE ONTO SCALP FOR SEVERAL MINUTES, AND THEN RINSE
- REPEAT IF DESIRED

INACTIVE INGREDIENTS

WATER (AQUA), SODIUM LAURETH SULFATE, ACRYLATES CROSSPOLYMER-4, COCAMIDE MEA, SODIUM COCOYL SARCOSINATE, GLYCOL DISTEARATE, POLYQUATERNIUM-7, FRARANCE (PARFUM), SODIUM CHLORIDE, SODIUM HYDROXIDE, TETRASODIUM EDTA, BHT, METHYLCHLOROISOTHIAZOLINONE, METHYLISOTHIAZOLINONE, BLUE 1 (CI 42090)

QUESTIONS OR COMMENTS?

1-866-695-3030